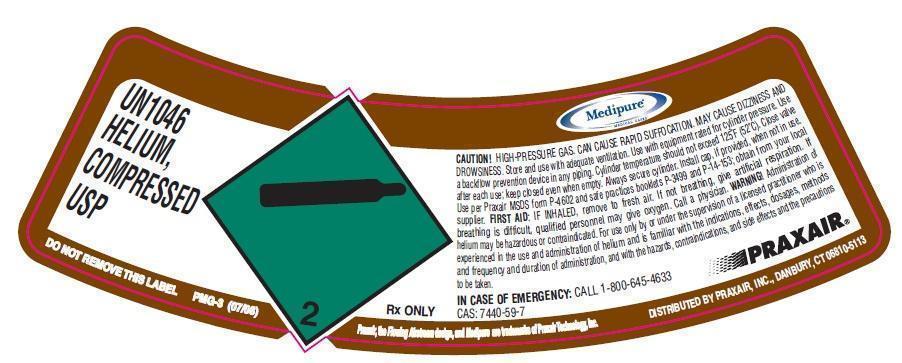 DRUG LABEL: Helium
NDC: 59579-015 | Form: GAS
Manufacturer: Praxair Distribution, Inc.
Category: animal | Type: PRESCRIPTION ANIMAL DRUG LABEL
Date: 20211221

ACTIVE INGREDIENTS: Helium 990 mL/1 L

Helium - Animal

Helium

UN1046 HELIUM, COMPRESSED USP CONTENTS LOT NUMBER CAUTION! HIGH-PRESSURE GAS. CAN CAUSE RAPID SUFFOCATION. MAY CAUSE DIZZINESS AND DROWSINESS. Store and use with adequate ventilation. Use with equipment rated for cylinder pressure. Use a backflow prevention device in any piping. Cylinder temperature should not exceed 125°F (52°C). Close valve after each use; keep closed even when empty. Always secure cylinder. Install cap, if provided, when not in use per Praxair MSDS form P-4602 and safe practices booklets P-3499 and P-14-153; obtain from your local supplier. FIRST AID: IF INHALED, remove to fresh air. If not breathing, give artificial respiration. If breathing is difficult, qualified personnel may give oxygen. Call a physician. WARNING! Administration of helium may be hazardous or contraindicated. For use only by or under the supervision of a licensed practitioner who is experienced in the use and administration of helium and is familiar with the indications, effects, dosages, methods and frequency and duration of administration, and with the hazards, contraindications, and side effects and the precautions to be taken. IN CASE OF EMERGENCY: CALL 1-800-645-4633 CAS: 7440-59-7 2 Rx ONLY DISTRIBUTED BY PRAXAIR, INC., DANBURY DO NOT REMOVE THIS LABEL PMG-3 (07/08) Praxair, the flowing airstream design and Medipure are trademarks of Praxair Technology, Inc. DISTRIBUTED BY PRAXAIR, INC, DANBURY, CT 06810-5113